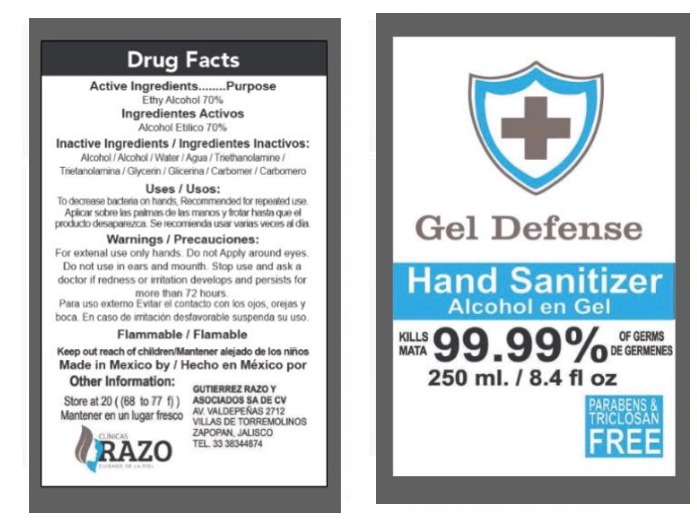 DRUG LABEL: HAND SANITIZER
NDC: 78770-4000 | Form: GEL
Manufacturer: GUTIERREZ RAZO Y ASOCIADOS, S.A. DE C.V.
Category: otc | Type: HUMAN OTC DRUG LABEL
Date: 20200617

ACTIVE INGREDIENTS: ALCOHOL 0.7 mL/1 mL
INACTIVE INGREDIENTS: TRIETHANOLAMINE CAPROYL GLUTAMATE 0.002 mL/1 mL; GLYCERIN 0.0375 mL/1 mL; CARBOMER 940 0.002 mL/1 mL; WATER 0.2585 mL/1 mL

HAND SANITIZER GEL DEFENSE

DOSAGE AND ADMINISTRATION

Directions

Place enough product on hands to cover all surfaces. Rub hands together until dry.

INACTIVE INGREDIENTS

Inactive ingredients Water (Aqua), Glycerin, Carbomer, Triethanolamine

USES

Use[s]

Hand Sanitizer to help reduce bacteria that potentially can cause disease. For use when soap and water are not available.

KEEP AWAY FROM CHILDREN

Keep out of reach of children. If swallowed, get medical help or contact a Poison Control Center right away.

PURPOSE

Purpose Antmicrobial

WARNINGS AND PRECAUTIONS

When using this product keep out of eyes, ears, and mouth. In case of contact with eyes, rinse eyes thoroughly with water.

WARNINGS

For external use only. Flammable. Keep away from heat or flame

ACTIVE INGREDIENT

Active ingredient. Ethyl Alcohol 70% v/v

ASK A DOCTO

Stop use and ask a doctor if irritation or rash occurs. These may be signs of a serious condition

STOP USE

Stop use and ask a doctor if irritation or rash occurs.